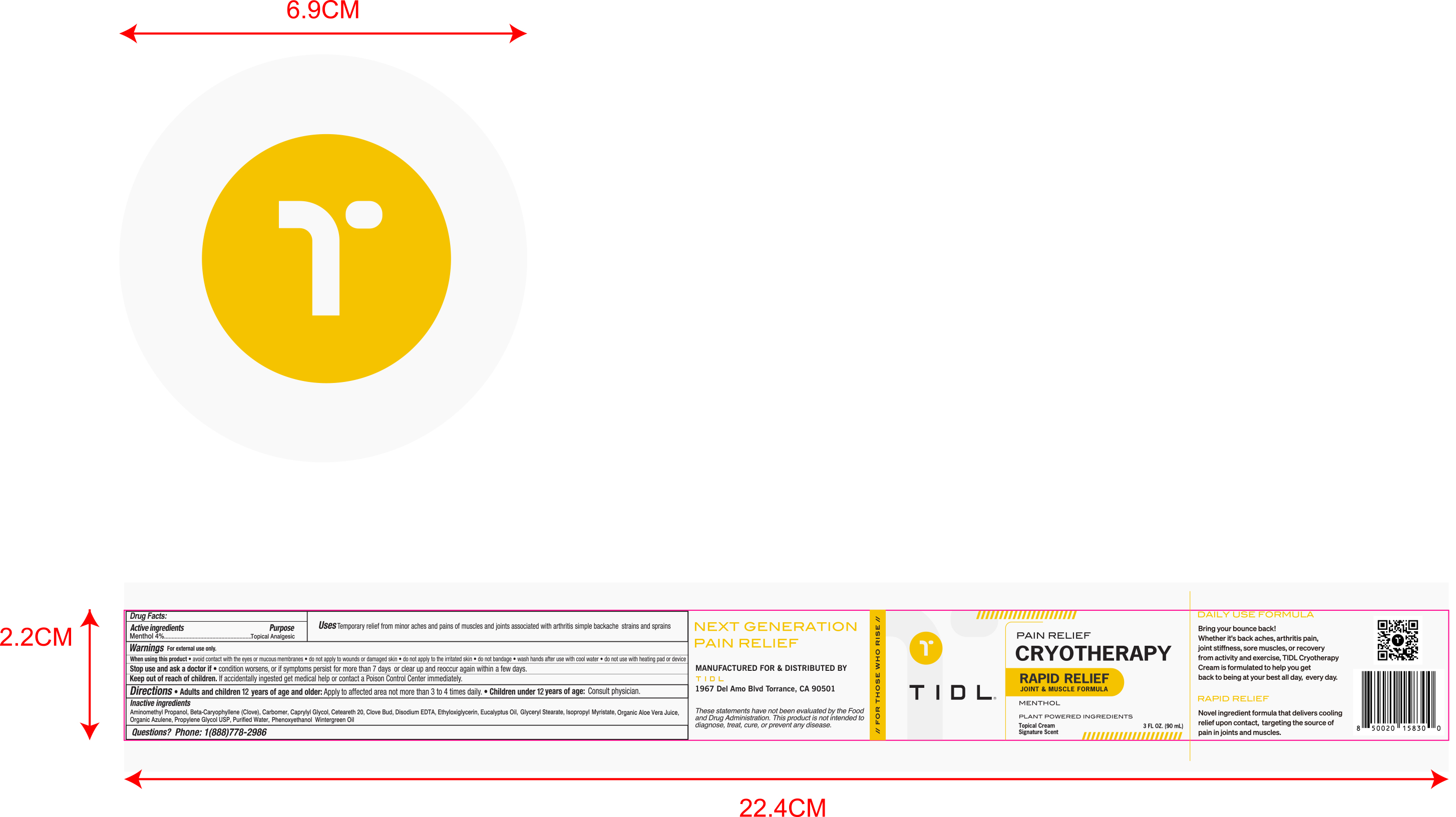 DRUG LABEL: TIDL PAIN RELIEF CRYOTHERAPY MENTHOL Cream
NDC: 84214-009 | Form: CREAM
Manufacturer: Shenzhen Sam Technology Co., Ltd.
Category: otc | Type: HUMAN OTC DRUG LABEL
Date: 20250905

ACTIVE INGREDIENTS: MENTHOL 4 g/100 mL
INACTIVE INGREDIENTS: ETHYLOXIRANE; PROPYLENE GLYCOL; AMINOMETHYL PROPANOL; WATER; GAULTHERIA PROCUMBENS (WINTERGREEN) LEAF OIL; EUCALYPTUS OIL; CAMPHOR OIL; EDETATE DISODIUM; PHENOXYETHANOL; CAPRYLYL GLYCOL; BETA-CARYOPHYLLENE; GLYCERYL STEARATE; ALOE VERA LEAF; CETEARETH-20; AZULENE; CARBOMER; ISOPROPYL MYRISTATE; CLOVE OIL

84214-009

Active Ingredient

Menthol 4%

Purpose

Topical Anesthetic

Use

Temporary relief from minor aches and pains of muscles and joints associated with arthritis simple backache strains and sprains

Warnings

For external use only

Do not use

·do not apply to wounds or damaged skin
·do not apply to irritated skin
·do not bandage
·do not use with heating pad or device

When Using

·avoid contact with the eyes or mucous membranes
·do not apply to wounds or damaged skin
·do not apply to irritated skin
·do not bandage
·wash hands after use with cool water
·do not use with heating pad or device

Stop Use

if condition worsens, or if symptoms persist for more than 7 days or clear up and reoccur again within a few days

Ask Doctor

if condition worsens, or if symptoms persist for more than 7 days or clear up and reoccur again within a few days

Keep Out Of Reach Of Children

If accidentally ingested get medical help or contact a Poison Control Center immediately.

Directions

·Adults and children 12 years of age and older：Apply to affected area not more than 3 to 4 times daily
·Children under 12 years of age：Consult physician

Inactive ingredients

Aminomethyl Propanol, Beta-Caryophyllene（Clove），Carbomer，Caprylyl Glycol，Ceteareth 20 ，
Clove Bud，Disodium EDTA ，Ethyloxiglycerin，Eucalyptus Oil，Glyceryl Stearate，Isopropyl Myristate，
Organic Aloe Vera Juice，Organic Azulene，Propylene Glycol USP，Purified Water，Phenoxyethanol，
Wintergreen Oil

Questions

Call 1（888）778-2986